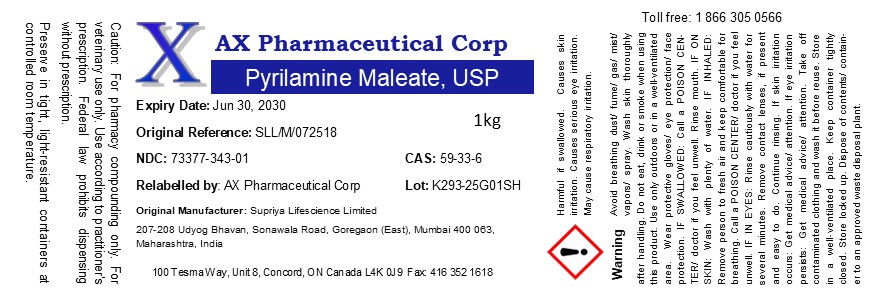 DRUG LABEL: Pyrilamine Maleate
NDC: 73377-343 | Form: POWDER
Manufacturer: AX Pharmaceutical Corp
Category: other | Type: BULK INGREDIENT - ANIMAL DRUG
Date: 20260119

ACTIVE INGREDIENTS: Pyrilamine Maleate 1 g/1 g

Pyrilamine Maleate